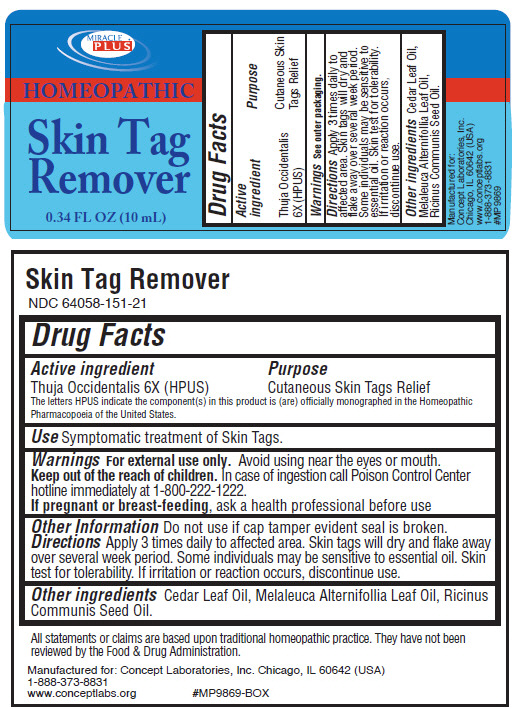 DRUG LABEL: Miracle Plus Homeopathic 
NDC: 64058-151 | Form: LIQUID
Manufacturer: Concept Laboratories, Inc.
Category: homeopathic | Type: HUMAN OTC DRUG LABEL
Date: 20141105

ACTIVE INGREDIENTS: THUJA OCCIDENTALIS LEAFY TWIG 6 [hp_X]/10 mL
INACTIVE INGREDIENTS: CEDAR LEAF OIL; TEA TREE OIL; CASTOR OIL

Miracle Plus® Homeopathic
Skin Tag Remover

Drug Facts

Active ingredient

Thuja Occidentalis 6X (HPUS)

The letters HPUS indicate the component(s) in this product is (are) officially monographed in the Homeopathic Pharmacopoeia of the United States.

Purpose

Cutaneous Skin Tags Relief

Use

Symptomatic treatment of Skin Tags.

Warnings

For external use only. Avoid using near the eyes or mouth.

KEEP OUT OF REACH OF CHILDREN

Keep out of the reach of children. In case of ingestion call Poison Control Center hotline immediately at 1-800-222-1222.

PREGNANCY OR BREAST FEEDING

If pregnant or breast-feeding, ask a health professional before use

Other Information

Do not use if cap tamper evident seal is broken.

Directions

Apply 3 times daily to affected area. Skin tags will dry and flake away over several week period. Some individuals may be sensitive to essential oil. Skin test for tolerability. If irritation or reaction occurs, discontinue use.

Other ingredients

Cedar Leaf Oil, Melaleuca Alternifollia Leaf Oil, Ricinus Communis Seed Oil.

PRINCIPAL DISPLAY PANEL - 10 mL Bottle Label

MIRACLE
PLUS®

HOMEOPATHIC

Skin Tag
Remover

0.34 FL OZ (10 mL)